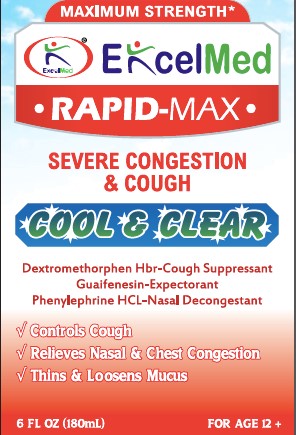 DRUG LABEL: Rapid Max Maximum Strength Cool and Clear - Cold, Severe Congestion and Cough
NDC: 71027-020 | Form: LIQUID
Manufacturer: KINGSTON PHARMA LLC
Category: otc | Type: HUMAN OTC DRUG LABEL
Date: 20170301

ACTIVE INGREDIENTS: DEXTROMETHORPHAN HYDROBROMIDE 20 mg/20 mL; GUAIFENESIN 400 mg/20 mL; PHENYLEPHRINE HYDROCHLORIDE 10 mg/20 mL
INACTIVE INGREDIENTS: CITRIC ACID MONOHYDRATE; DEXTROSE, UNSPECIFIED FORM; METHYL SALICYLATE; GLYCERIN; METHYLPARABEN; POTASSIUM SORBATE; PROPYLENE GLYCOL; PROPYLPARABEN; WATER; D&C RED NO. 33; FD&C RED NO. 40; SACCHARIN SODIUM; SODIUM HYDROXIDE; SUCRALOSE; XANTHAN GUM

ExcelMed Rapid Max Maximum Strength Cool & Clear- Cold, Severe Congestion & Cough

Active Ingredient: Each 20ml contains:
Dextromethorphan 20 mg
Guaifenesin 400 mg
Phenylephrine 10 mg

Purpose:
Pain reliever, Fever Reducer
Cough Suppressant
Expectorant
Nasal Decongestant

Uses

- Temporarily relieves these common cold/flu symptoms
  1. Minor aches and pains
  2. Headache
  3. Sore throat
  4. Nasal congestion
  5. Fever
  6. Cough due to minor throat and bronchial irritation

DO NOT USE IF PRINTED SAFETY SEAL ON THE BOTTLE IS BROKEN OR MISSING.

Warnings:

Do not use

- if you are now taking a prescription monoamine oxidase inhibitor (MAOI) (certain drugs for depression, psychiatric or emotional conditions, or Parkinson's disease), or for 2 weeks after stopping the MAOI drug. If you do not know if your prescription drug contains an MAOI, ask a doctor or pharmacist before taking this product.
- If you have ever had an allergic reaction to this product or any of its ingredients.

Ask a doctor before use if you have

- Liver disease
- Heart disease
- High blood pressure
- Thyroid disease
- Diabetes
- Trouble urinating due to an enlarged prostate gland
- Persistent or chronic cough such as occurs with smoking, asthma, chronic bronchitis or emphysema
- Cough that occurs with too much phlegm (mucus)
- A Sodium restricted diet

Ask a doctor or pharmacist before use if you are

- Taking the blood thinning drug warfarin

When using this product

- Do not exceed recommended dosage (see overdose warning)

Stop use and ask doctor if

- Nervousness, dizziness or sleeplessness occur
- Symptoms get worse or last more than 5 days (children) or 7 days (adults)
- Fever gets worse or lasts more than 3 days
- Redness or swelling is present
- New symptoms occur
- Cough comes back or occurs with rash or headache that lasts

These could be signs of a serious condition

KEEP OUT OF REACH OF CHILDREN

Keep this and all drugs out of the reach of children.

Overdose Warning: In case of accidental overdose, seek professional assistance or contact a Poison control center right away. Quick medical attention is critical for adults as well as children even if you do not notice any signs or symptoms.

If pregnant or breast-feeding,
ask a health professional before use.

Directions:

- Do not take more than directed. (see overdose warning)
- Use enclosed dosing cup.
- Do not take more than 4 doses in 24-hours.
- Adults and children 12 years and over: take 20 mL every 4 hours.
- Children under 12 years: do not use

Other information

- Store between 20-25 degree Celsius (68-77 degree Fahrenheit)
- Each tablespoon contains: Sodium 13mg

INACTIVE INGREDIENT

Inactive ingredients citric acid, dextrose, flavors, glycerin, methyl paraben, potassium sorbate, propylene glycol, propyl paraben, purified water, red 33, red 40, saccharin sodium, sodium hydroxide, sucralose, xanthan gum

HOW SUPPLIED

(packs: 6oz) Kingston NDC# 71027-020-06

Manufactured by: Kingston Pharma LLC
5 County Route 42
Massena, NY 13662